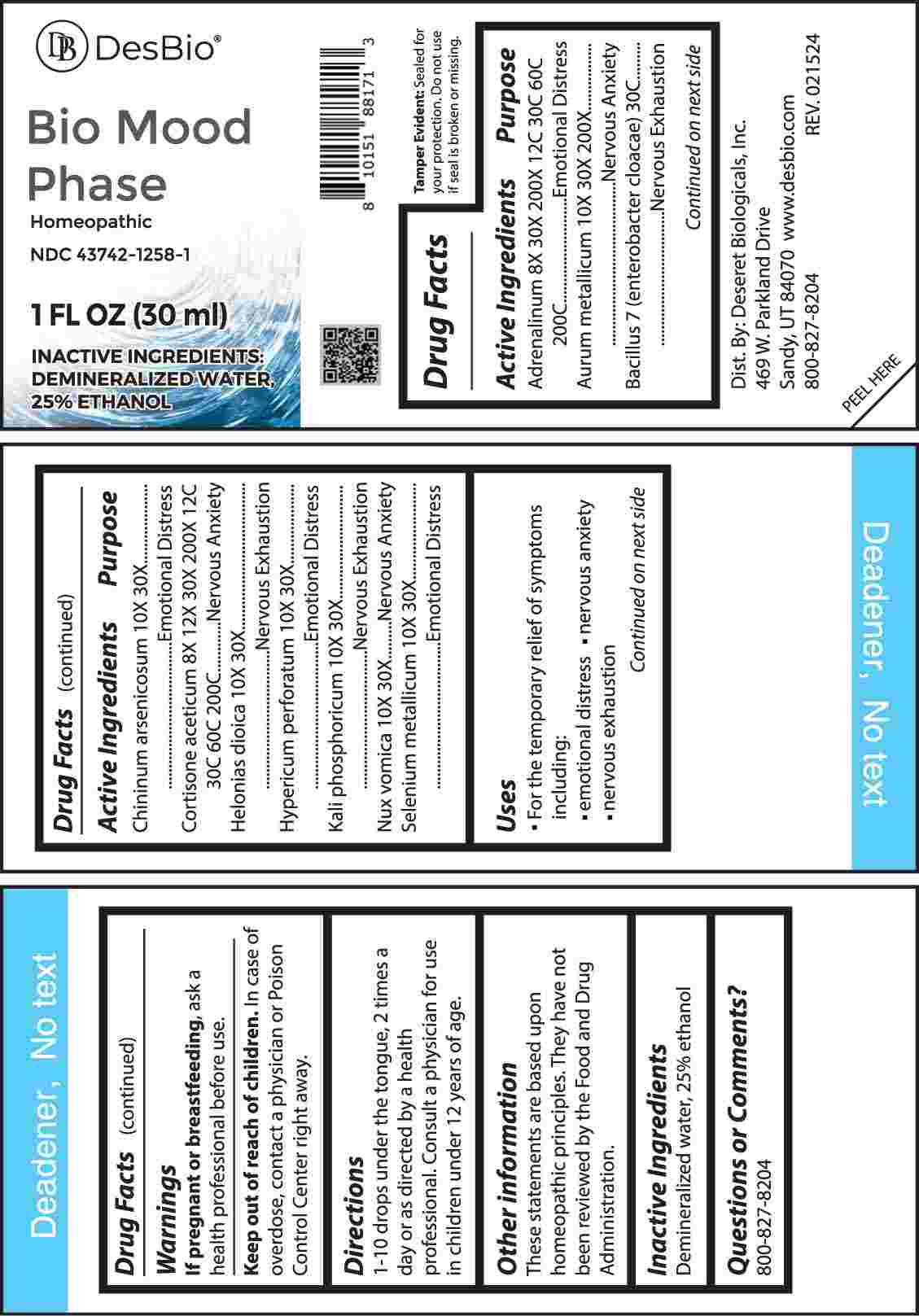 DRUG LABEL: Bio Mood Phase
NDC: 43742-1258 | Form: LIQUID
Manufacturer: Deseret Biologicals, Inc.
Category: homeopathic | Type: HUMAN OTC DRUG LABEL
Date: 20240426

ACTIVE INGREDIENTS: CORTISONE ACETATE 8 [hp_C]/1 mL; EPINEPHRINE 8 [hp_C]/1 mL; QUININE ARSENATE 10 [hp_C]/1 mL; CHAMAELIRIUM LUTEUM ROOT 10 [hp_C]/1 mL; HYPERICUM PERFORATUM WHOLE 10 [hp_C]/1 mL; DIBASIC POTASSIUM PHOSPHATE 10 [hp_C]/1 mL; STRYCHNOS NUX-VOMICA SEED 10 [hp_C]/1 mL; SELENIUM 10 [hp_C]/1 mL; GOLD 10 [hp_C]/1 mL; ENTEROBACTER CLOACAE 30 [hp_C]/1 mL
INACTIVE INGREDIENTS: WATER; ALCOHOL

DRUG FACTS:

ACTIVE INGREDIENTS:

Adrenalinum 8X, 30X, 200X, 12C, 30C, 60C, 200C, Aurum Metallicum 10X, 30X, 200X, Bacillus 7 (Enterobacter Cloacae) 30C, Chininum Arsenicosum 10X, 30X, Cortisone Aceticum 8X, 12X, 30X, 200X, 12C, 30C, 60C, 200C, Helonias Dioica 10X, 30X, Hypericum Perforatum 10X, 30X, Kali Phosphoricum 10X, 30X, Nux Vomica 10X, 30X, Selenium Metallicum 10X, 30X.

PURPOSE:

Adrenalinum – Emotional Distress, Aurum Metallicum – Nervous Anxiety, Bacillus 7 (Enterobacter Cloacae) – Nervous Exhaustion, Chininum Arsenicosum – Emotional Distress, Cortisone Aceticum – Nervous Anxiety, Helonias Dioica – Nervous Exhaustion, Hypericum Perforatum – Emotional Distress, Kali Phosphoricum – Nervous Anxiety, Nux Vomica – Nervous Anxiety, Selenium Metallicum – Emotional Distress

USES:

• For the temporary relief of symptoms including:

• emotional distress • nervous anxiety • nervous exhaustion

These statements are based upon homeopathic principles. They have not been reviewed by the Food and Drug Administration.

WARNINGS:

If pregnant or breast-feeding, ask a health professional before use.

Keep out of reach of children. In case of overdose, contact a physician or Poison Control Center right away.

Tamper Evident: Sealed for your protection. Do not use if seal is broken or missing.

KEEP OUT OF REACH OF CHILDREN:

In case of overdose, contact a physician or Poison Control Center right away.

DIRECTIONS:

1-10 drops under the tongue, 2 times a day or as directed by a health professional. Consult a physician for use in children under 12 years of age.

INACTIVE INGREDIENTS:

Demineralized water, 25% ethanol

QUESTIONS:

Dist. By: Deseret Biologicals, Inc.

469 W. Parkland Drive

Sandy, UT 84070

www.desbio.com

800-827-8204

PACKAGE LABEL DISPLAY:

Des Bio

Bio Mood Phase

Homeopathic

NDC 43742-1258-1

1 FL OZ (30 ml)